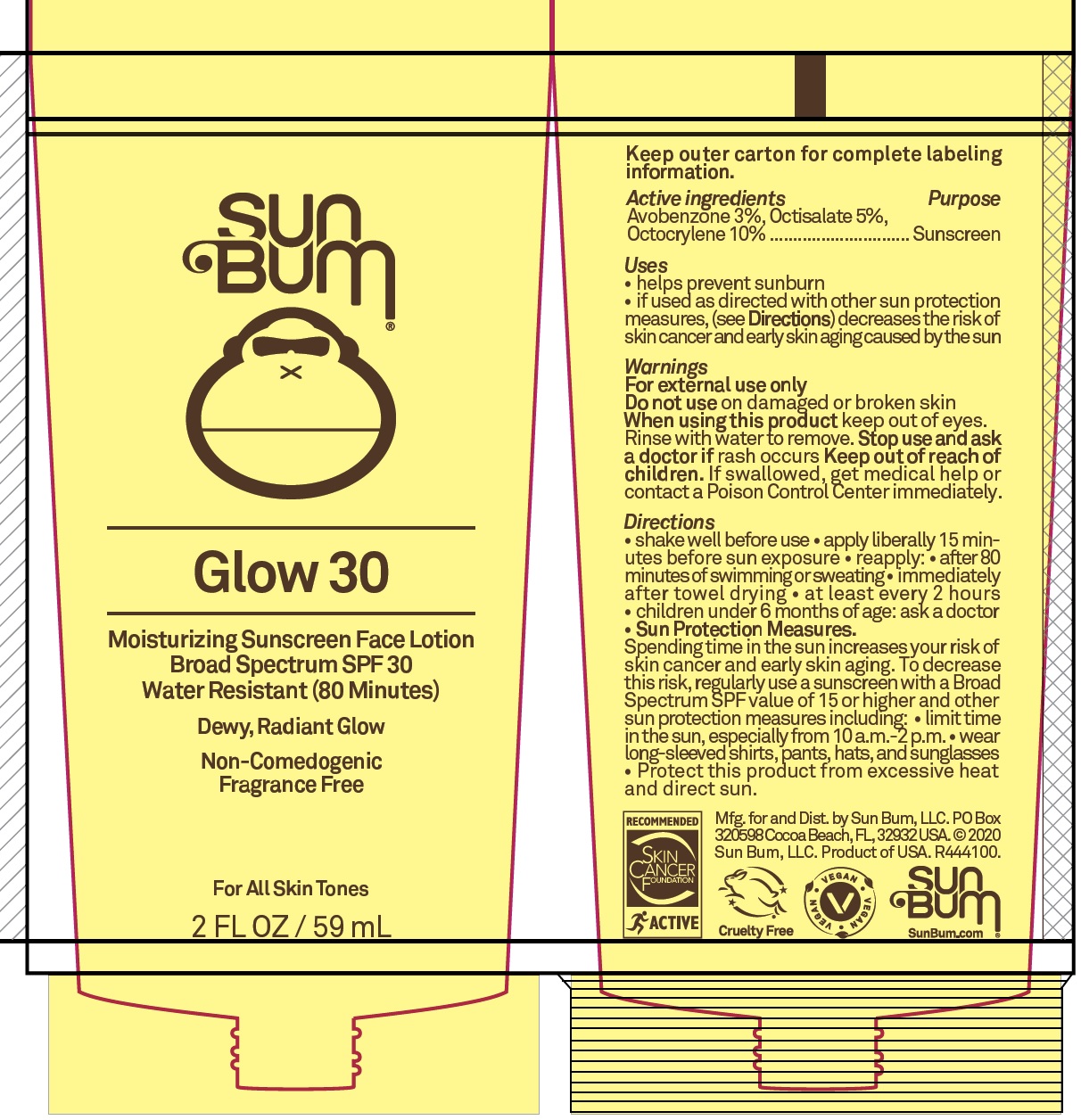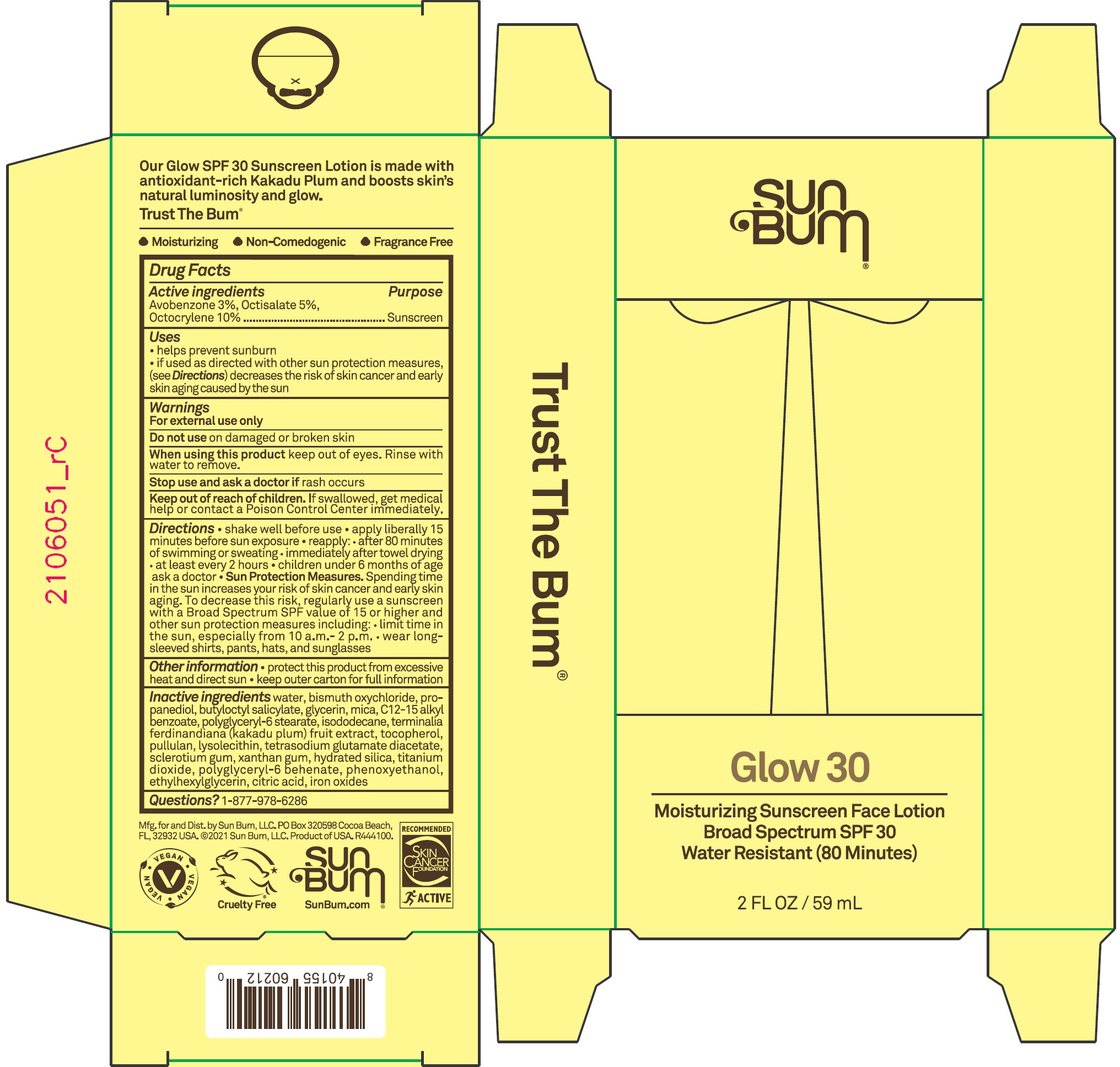 DRUG LABEL: Sun Bum GLOW 30 Moisturizing Sunscreen Face SPF 30
NDC: 69039-640 | Form: LOTION
Manufacturer: Sun Bum LLC
Category: otc | Type: HUMAN OTC DRUG LABEL
Date: 20220204

ACTIVE INGREDIENTS: AVOBENZONE 30 mg/1 mL; OCTISALATE 50 mg/1 mL; OCTOCRYLENE 100 mg/1 mL
INACTIVE INGREDIENTS: WATER; BISMUTH OXYCHLORIDE; PROPANEDIOL; BUTYLOCTYL SALICYLATE; GLYCERIN; MICA; ALKYL (C12-15) BENZOATE; POLYGLYCERYL-6 STEARATE; ISODODECANE; KAKADU PLUM; TOCOPHEROL; PULLULAN; LYSOPHOSPHATIDYLCHOLINE, SOYBEAN; TETRASODIUM GLUTAMATE DIACETATE; BETASIZOFIRAN; XANTHAN GUM; HYDRATED SILICA; TITANIUM DIOXIDE; POLYGLYCERYL-6 BEHENATE; PHENOXYETHANOL; ETHYLHEXYLGLYCERIN; CITRIC ACID MONOHYDRATE; FERRIC OXIDE RED

Sun Bum GLOW 30 Moisturizing Sunscreen Face Lotion SPF 30

Active ingredients

Avobenzone 3%,
Octisalate 5%,
Octocrylene 10%

Purpose

Sunscreen

Uses

- helps prevent sunburn
- if used as directed with other sun protection measures, (see Directions) decreases the risk of skin cancer and early skin aging caused by the sun

Warnings

For external use only

Do not use

on damaged or broken skin

When using this product

keep out of eyes. Rinse with water to remove.

Stop use and ask a doctor if

rash occurs

Keep out of reach of children.

If swallowed, get medical help or contact a Poison Control Center immediately.

Directions

• shake well before use • apply liberally 15 minutes before sun exposure • reapply: • after 80 minutes of swimming or sweating • immediately after towel drying • at least every 2 hours • children under 6 months of age: ask a doctor • Sun Protection Measures. Spending time in the sun increases your risk of skin cancer and early skin aging. To decrease this risk, regularly use a sunscreen with a Broad Spectrum SPF value of 15 or higher and other sun protection measures including: • limit time in the sun, especially from 10 a.m.-2 p.m. • wear long-sleeved shirts, pants, hats, and sunglasses

Other information

• protect this product from excessive heat and direct sun • keep outer carton for full information

Inactive ingredients

water, bismuth oxychloride, propanediol, butyloctyl salicylate, glycerin, mica, C12-15 alkyl benzoate, polyglyceryl-6 stearate, isododecane, terminalia ferdinandiana (kakadu plum) fruit extrat, tocopherol, pullulan, lysolecithin, tetrasodium glutamate diacetate, sclerotium gum, xanthan gum, hydrated silica, titanium dioxide, polyglyceryl-6 behenate, phenoxyethanol, ethylhexylglycerin, citric acid, iron oxide

Questions?

1-877-978-6286